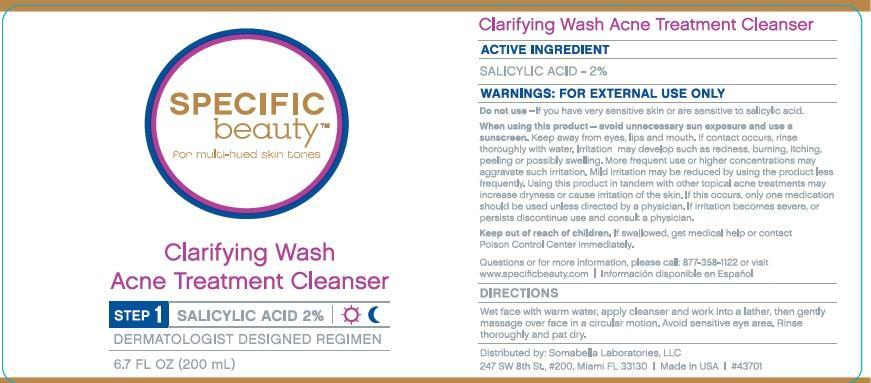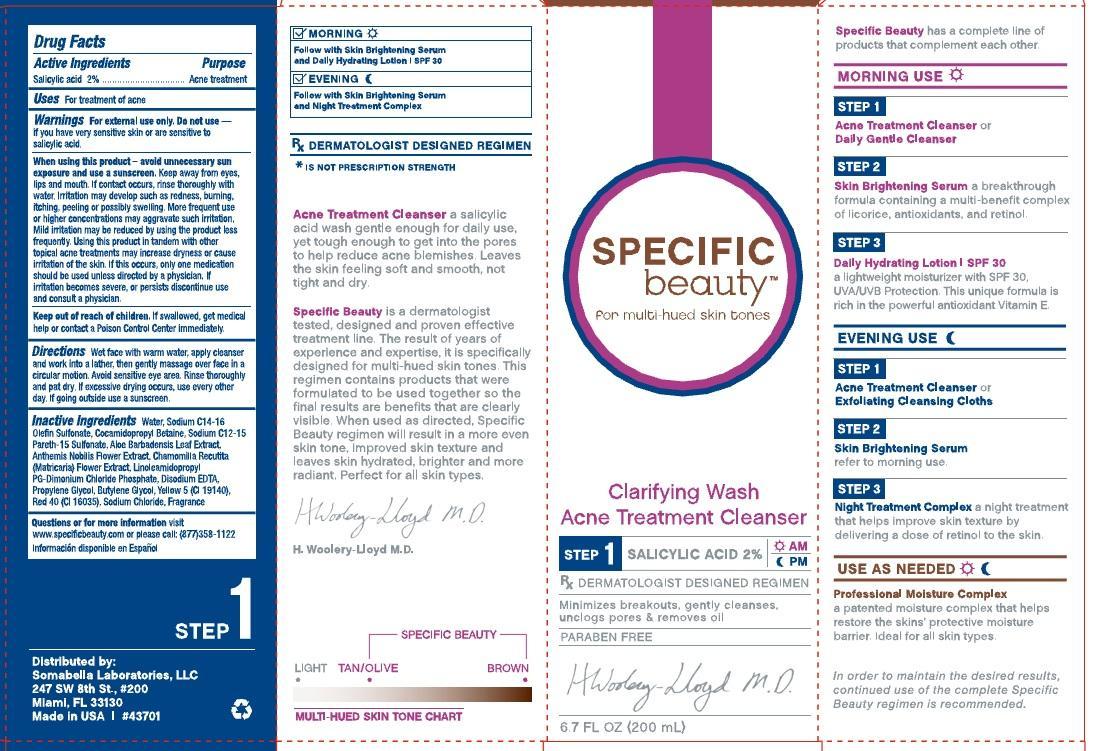 DRUG LABEL: Specific Beauty Clarifying Wash Acne Treatment Cleanser
NDC: 52295-207 | Form: SOAP
Manufacturer: Somabella Laboratories, LLC
Category: otc | Type: HUMAN OTC DRUG LABEL
Date: 20190404

ACTIVE INGREDIENTS: SALICYLIC ACID 20 mg/1 mL
INACTIVE INGREDIENTS: WATER; SODIUM C14-16 OLEFIN SULFONATE; COCAMIDOPROPYL BETAINE; SODIUM C12-15 PARETH-15 SULFONATE; ALOE VERA LEAF; CHAMAEMELUM NOBILE FLOWER; CHAMOMILE; LINOLEAMIDOPROPYL PG-DIMONIUM CHLORIDE PHOSPHATE; EDETATE DISODIUM; PROPYLENE GLYCOL; BUTYLENE GLYCOL; FD&C YELLOW NO. 5; SODIUM CHLORIDE

Specific Beauty Clarifying Wash Acne Treatment Cleanser

Active Ingredients

Salicylic Acid 2%

Purpose

Acne Treatment

Uses

For treatment of acne

Warnings

For external use only. Do not use if you have very sensitive skin or are sensitive to salicylic acid.

When using this product -

avoid unnecessary sun exposure and use a sunscreen. Keep away from eyes lips and mouth. If contact occurs, rinse thoroughly with water. Irritation may develop such as redness, burning, itching peeling or possibly swelling. More frequent use or higher concentrations may aggravate such irritation. Mild irritation may be reduced by using the product less frequently. using this product in tandem with other topical acne treatments may increase dryness or cause irritation of the skin. If this occurs, only one medication should be used unless directed by a physician. If irritation becomes severe, or persists, discontinue use and consult a physician.

Keep out of reach of children.

If swallowed, get medical help or contact a Poison Control Center immediately.

Directions

Wet face with warm water, apply cleanser and work into a lather, then gently massage over face in a circular motion. Avoid sensitive eye area. Rinse thoroughly and pat dry. If excessive drying occurs, use every other day. If going outside use a sunscreen.

Inactive Ingredients

Water, Sodium C14-16 Olefin Sulfonate, Cocamidopropryl Betaine, Sodium C12-15 Pareth-15 Sulfonate, Aloe Barbadensis Leaf Extract, Anthemis Nobilis flower extract, Chamomilla Recutita (Matricaria) Flower Extract, Linoleamidopropyl PG-Dimonium Chloride Phosphate, Disodium EDTA, Propylene Glycol, Butylene Glycol, Yellow 5 (CI191440), Red 40 (CI 16035), Sodium Chloride, Fragrance.

Questions or for more information

visit www.specificbeauty.com or please call: (877) 358-1122

Information disponable en Espanol

DESCRIPTION

Morning

Follow with Skin Brightening Serum and Daily Hydrating Lotion SPF 30

Evening Follow with Skin Brightening Serum and Night Treatment Complex

Rx Dermatologist designed regimen
*is not prescription strength
Acne Treatment Cleanser a salicylic acid wash gentle enough for daily use, yet tough enough to get into the pores to help reduce acne blemishes. Leaves the skin feeling soft and smooth, not tight and dry.
Specific Beauty is a dermatologist tested, designed and proven effective treatment line. The result of years of experience and expertise, it is specifically designed for multi-hued skin tones. This regimen contains products that were formulated to be used together so the final results are benefits that are clearly visible. When used as directed, Specific Beauty regimen will result in a more even skin tone, improved skin texture and leaves skin hydrated, brighter and more radiant. Perfect for all skin types.
H. Woolery-Lloyd, M.D.
Specific Beauty has a complete line of products that compliment each other
MORNING USE
STEP 1
Acne Treatment Cleanser or Daily Gentle Cleanser
S TEP 2
Skin Brightening Serum a breakthrough formula containing a multi-benefit complex of licorice, antioxidants and retinol
STEP 3
Daily Hydrating Lotion | SPF 30 A lightweight moisturizer with SPF 30, UVA/UVB Protection. This unique formula is rich in the powerful antioxidant Vitamin E.
EVENING USE
STEP 1
Acne Treatment Cleanser or Exfoliating Cleansing Cloths
STEP 2
Skin Brightening Serum
refer to morning use.
STEP 3
Night Treatment Complex a night treatment that helps improve skin texture by delivering a dose of retinol to the skin.
USE AS NEEDED
Professional Moisture Complex
a patented moisture complex that helps restore the skins' protective moisture barrier. Ideal for all skin types.
In order to maintain the desired results, continued use of the complete Specific Beauty regimen is recommended.

PACKAGE LABEL

Specific Beauty

for multi-hued skin tones

Clarifying Wash

Acne Treatment Cleansr

Step 1 Salicylic Acid 2% AM/PM

Rx Dermatologist Designed Regimen

Minimizes breakouts, gently cleanses, unclogs pores, and removes oil

PARABEN FREE